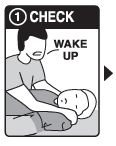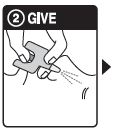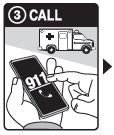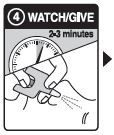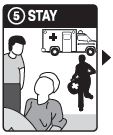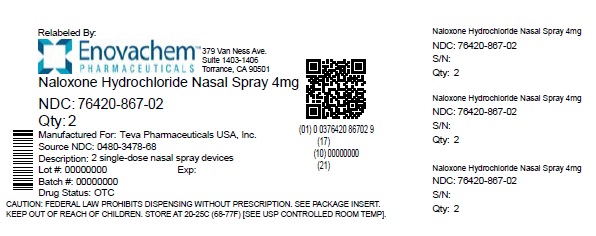 DRUG LABEL: Naloxone Hydrochloride
NDC: 76420-867 | Form: SPRAY, METERED
Manufacturer: Asclemed USA, Inc.
Category: otc | Type: HUMAN OTC DRUG LABEL
Date: 20241029

ACTIVE INGREDIENTS: NALOXONE HYDROCHLORIDE 4 mg/0.1 mL
INACTIVE INGREDIENTS: BENZALKONIUM CHLORIDE; EDETATE DISODIUM; SODIUM CHLORIDE; HYDROCHLORIC ACID; WATER

Drug Facts

Active ingredient (in each spray)

Naloxone hydrochloride 4 mg

Purpose

Emergency treatment of opioid overdose

Uses

- to “revive” someone during an overdose from many prescription pain medicationsor street drugs such as heroin
- this medicine can save a life

Directions

Step 1: CHECK if you suspect an overdose:

- CHECKfor a suspected overdose:the person will not wake up or is very sleepy or not breathing well
- yell “Wake up!”
- shake the person gently
- if the person is not awake, go to Step 2

Step 2: GIVE 1stdose in the nose

- HOLDthe nasal spray device with your thumb on the bottom of the plunger
- INSERTthe nozzle into either NOSTRIL
- PRESSthe plunger firmly to give the 1stdose
- 1 nasal spray device contains 1 dose

Step 3: CALL

- CALL 911immediately after giving the 1stdose

Step 4: WATCH & GIVE

- WAIT2-3 minutes after the 1stdose to give the medicine time to work
- if the person wakes up:Go to Step 5
- if the person does not wake up:

- CONTINUE TO GIVEdoses every 2-3 minutes until the person wakes up
- it is safe to keep giving doses

Step 5: STAY

- STAYuntil ambulance arrives: even if the person wakes up
- GIVEanother dose if the person becomes very sleepy again
- You may need to give all the doses in the pack

Warning

- When using this productsome people may experience
  symptoms when they wake up, such as, shaking, sweating,
  nausea, or feeling angry. This is to be expected.

Other information

- Store below 77°F (25°C).
- do not freeze
- avoid excessive heat above 40°C (104°F)
- protect from light
- the product is packaged in individually-sealed blisters.
  Do not use if the blister is open or torn, or if the device appears damaged.

Inactive Ingredients

benzalkonium chloride, edetate disodium, sodium chloride buffered with sodium hydroxide/hydrochloric acid, water

Questions?

1-888-838-2872 between 9 am and 5 pm ET, Monday-Friday.
www.tevausa.com/our-products/tevagenerics

Safe to Use
Even if Opioids are Not Present

*This product is not affiliated with, manufactured by, or produced by
the makers or owners of NARCAN®

Relabeled by:

Enovachem PHARMACEUTICALS

Torrance, CA 90501